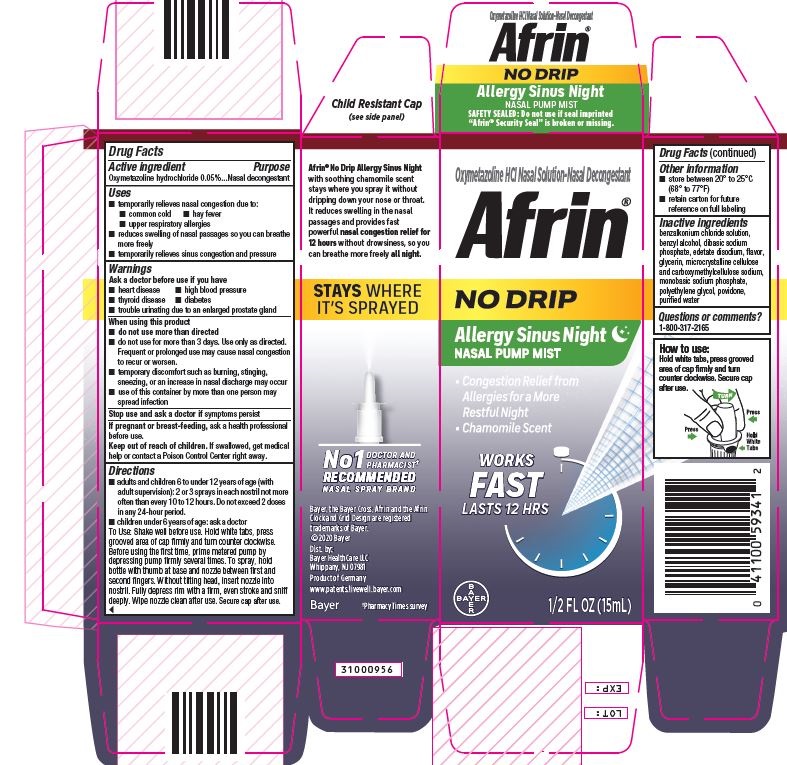 DRUG LABEL: Afrin NoDrip Allergy Sinus Night
NDC: 11523-0034 | Form: SPRAY
Manufacturer: Bayer HealthCare LLC.
Category: otc | Type: HUMAN OTC DRUG LABEL
Date: 20251204

ACTIVE INGREDIENTS: OXYMETAZOLINE HYDROCHLORIDE 0.5 mg/1 mL
INACTIVE INGREDIENTS: CARBOXYMETHYLCELLULOSE SODIUM; SODIUM PHOSPHATE, MONOBASIC; WATER; EDETATE DISODIUM; GLYCERIN; BENZALKONIUM CHLORIDE; POVIDONE; POLYETHYLENE GLYCOL, UNSPECIFIED; BENZYL ALCOHOL; MICROCRYSTALLINE CELLULOSE; HIBISCUS BIFURCATUS WHOLE

Afrin NoDrip Allergy Sinus Night UI1612461

Drug Facts

Active ingredient Purpose

Oxymetazoline hydrochloride 0.05%…….…....Nasal decongestant

Uses

▪ temporarily relieves nasal congestion due to:

▪ common cold ▪hay fever

▪ upper respiratory allergies

▪ reduces swelling of nasal passages so you can breathe more freely

▪ temporarily relieves sinus congestion and pressure

Warnings

▪ Ask a doctor before use if you have

▪ heart disease • high blood pressure

▪ thyroid disease ▪ diabetes

▪ trouble urinating due to an enlarged prostate gland

When using this product

▪ do not use more than directed

▪ do not use for more than 3 days. Use only as directed.

Frequent or prolonged use may cause nasal congestion to

recur or worsen.

▪ temporary discomfort such as burning, stinging, sneezing, or an

increase in nasal discharge may occur

▪ use of this container by more than one person may spread

infection

Stop use and ask a doctor if symptoms persist

PREGNANCY OR BREAST FEEDING

If pregnant or breast-feeding, ask a health professional before use.

Keep out of reach of children. If swallowed, get medical help or contact a Poison Control Center right away.

Directions

▪ adults and children 6 to under 12 years of age (with adult

supervision): 2 or 3 sprays in each nostril not more often than

every 10 to 12 hours. Do not exceed 2 doses in any 24-hour

period.

▪ children under 6 years of age: ask a doctor

To Use: Shake well before use. Hold white tabs, press grooved area of cap firmly and turn counter clockwise. Before using the first time, prime metered pump by depressing pump firmly several times. To spray, hold bottle with thumb at base and nozzle between first and second fingers. Without tilting head, insert nozzle into nostril. Fully depress rim with a firm, even stroke and sniff deeply. Wipe nozzle clean after use. Secure cap after use.

Other information

▪ store between 20º to 25ºC (68º to 77ºF)

▪ retain carton for future reference on full labeling

INACTIVE INGREDIENT

Inactive ingredients benzalkonium chloride solution, benzyl alcohol, dibasic sodium phosphate, edetate disodium, flavor, glycerin, microcrystalline cellulose and carboxymethylcellulose sodium, monobasic sodium phosphate, polyethylene glycol, povidone, purified water

Questions or comments? 1-800-317-2165

Carton label 15 mL

Oxymetazoline HCl

Nasal Solution-Nasal Decongestant

AFRIN

NODRIP

Wont drive from nose or down throat

Allergy Sinus

Night

with soothing chamomile scent

PUMP MIST

Instant Congestion

Relief from Allergies

for a More Restful Night

Reduces

Swelling of

Nasal

Passages

1/2 FL OZ (15mL)